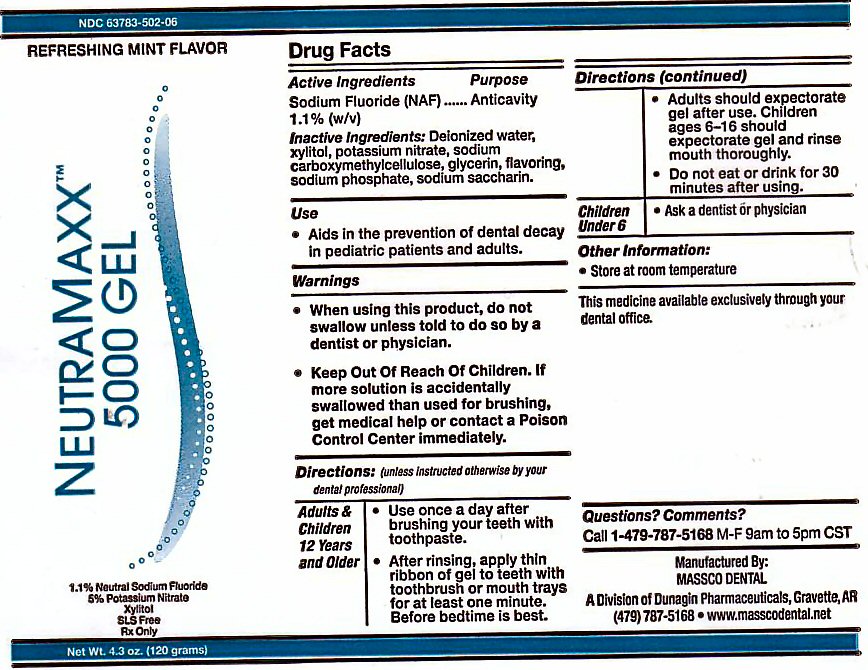 DRUG LABEL: NEUTRA MAXX 5000
NDC: 63783-504 | Form: GEL
Manufacturer: Massco Dental A Division of Dunagin Pharmaceuticals
Category: prescription | Type: HUMAN PRESCRIPTION DRUG LABEL
Date: 20231217

ACTIVE INGREDIENTS: SODIUM FLUORIDE 1.428 g/120 g
INACTIVE INGREDIENTS: WATER; XYLITOL; POTASSIUM NITRATE; CARBOXYMETHYLCELLULOSE SODIUM; GLYCERIN; SODIUM PHOSPHATE; SACCHARIN SODIUM

ACTIVE INGREDIENTS

ACTIVE INGREDIENT PURPOSE
SODIUM FLUORIDE (NaF) 1.1% (w/v) ANTICAVITY
INACTIVE INGREDIENTS
DEIONIZED WATER, XYLITOL, POTASSIUM NITRATE, SODIUM CARBOXYMETHYLCELLOSE, GLYCERIN, FLAVORING,SODIUM SACCHARIN, SODIUM PHOSPHATE .

USE

USE: AIDS IN THE PREVENTION OF DENTAL DECAY IN PEDIATRIC PATIENTS AND ADULTS

KEEP OUT OF REACH OF CHILDREN. IF MORE SOLUTION IS ACCIDENTALLY SWALLOWED THAN USED FOR BRUSHING, GET MEDICAL HELP OR CONTACT A POISON CONTROL CENTER IMMEDIATELY.

DIRECTIONS

DIRECTIONS: (UNLESS INSTRUCTED OTHERWISE BY YOUR DENTAL PROFESSIONAL)
ADULTS AND CHILDREN 6 YEARS AND OLDER: USE ONCE A DAY AFTER BRUSHING TEETH WITH TOOTHPASTE. AFTER RINSING, APPLY THIN RIBBON OF GEL TO TEETH WITH TOOTHBRUSH OR MOUTH TRAYS FOR AT LEASE ONE MINUTE. BEFORE BEDTIME IS BEST. ADULTS SHOULD EXPECTORATE AFTER USE. CHILDREN AGES 6-16 SHOULD EXPECTORATE GEL AND RINSE MOUTH THOROUGHLY. DO NOT EAT OR DRINK FOR 30 MINUTES AFTER USE.

WARNINGS

WHEN USING THIS PRODUCT DO NOT SWALLOW UNLESS TOLD TO DO SO BY A DENTIST OR PHYSICIAN.

PACKAGE LABEL

NEUTRA MAXX 5000PPM GEL REFRESHING MINT FLAVOR
THE MAXIMUM AMOUNT OF FLUORIDE AVAILABLE 1.1% SODIUM FLUORIDE 5% POTASSIUM NITRATE XYLITOL SLS FREE Rx ONLY. NET WT 4.3 oz (120 g)
MANUFACTURED BY MASSCO DENTAL A DIVISION OF DUNAGIN PHARMACEUTICALS GRAVETTE, AR 72736 THE MEDICINE AVAILABLE EXCLUSIVELY THROUGH YOUR DENTAL OFFICE.

OTHER INFORMATION: STORE AT ROOM TEMPERATURE QUESTION? COMMENTS? CALL 1-479-787-5168 M-F 9AM TO 5PM CST